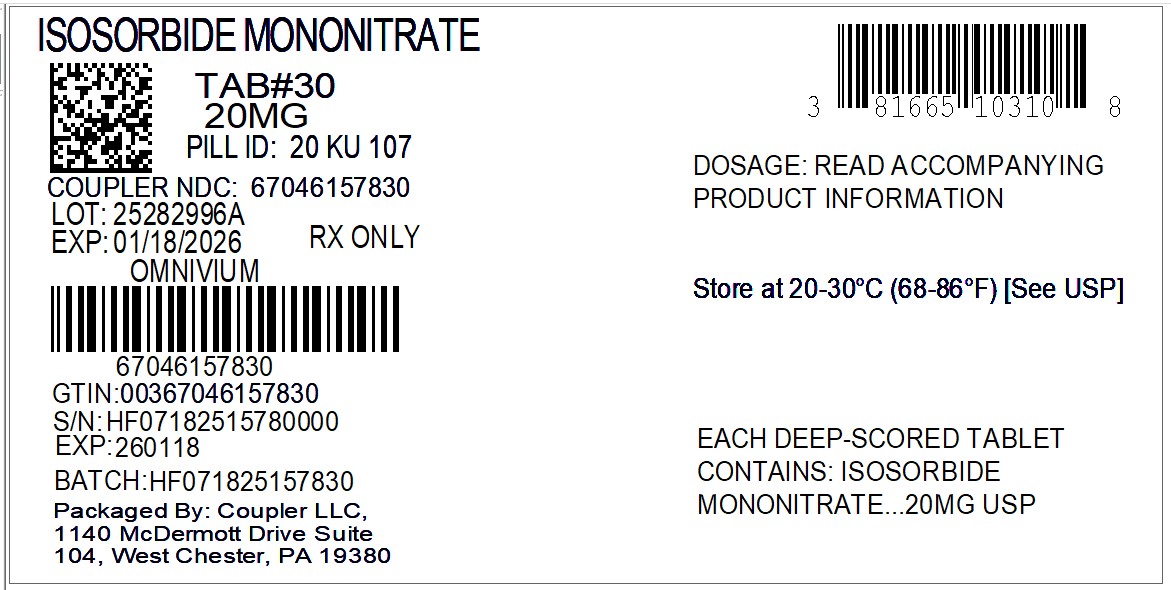 DRUG LABEL: isosorbide mononitrate
NDC: 67046-1578 | Form: TABLET
Manufacturer: Coupler LLC
Category: prescription | Type: HUMAN PRESCRIPTION DRUG LABEL
Date: 20250905

ACTIVE INGREDIENTS: ISOSORBIDE MONONITRATE 20 mg/1 1
INACTIVE INGREDIENTS: LACTOSE, UNSPECIFIED FORM; TALC; SILICON DIOXIDE; CELLULOSE, MICROCRYSTALLINE; ALUMINUM STEARATE

Isosorbide Mononitrate Tablets, USP

Rx Only

DESCRIPTION:

Isosorbide mononitrate, an organic nitrate, is a vasodilator with effects on both arteries and veins. The empirical formula is C6H9NO6and the molecular weight is 191.14. The chemical name for isosorbide mononitrate is 1,4:3,6-Dianhydro-D-glucitol 5-nitrate and the compound has the following structural formula:

Isosorbide Mononitrate Tablets, USP are available as 10 mg and 20 mg tablets. Each tablet also contains as inactive ingredients: lactose, talc, colloidal silicon dioxide, starch, microcrystalline cellulose and aluminum stearate.

CLINICAL PHARMACOLOGY:

Isosorbide mononitrate is the major active metabolite of isosorbide dinitrate (ISDN), and most of the clinical activity of the dinitrate is attributable to the mononitrate.

The principal pharmacological action of isosorbide mononitrate is relaxation of vascular smooth muscle and consequent dilatation of peripheral arteries and veins, especially the latter. Dilation of the veins promotes peripheral pooling of blood and decreases venous return to the heart, thereby reducing left ventricular end-diastolic pressure and pulmonary capillary wedge pressure (preload). Arteriolar relaxation reduces systemic vascular resistance, systolic arterial pressure, and mean arterial pressure (afterload). Dilatation of the coronary arteries also occurs. The relative importance of preload reduction, afterload reduction and coronary dilatation remains undefined.

Pharmacodynamics:

Dosing regimens for most chronically used drugs are designed to provide plasma concentrations that are continuously greater than a minimally effective concentration. This strategy is inappropriate for organic nitrates. Several well-controlled clinical trials have used exercise testing to assess the antianginal efficacy of continuously-delivered nitrates. In the large majority of these trials, active agents were indistinguishable from placebo after 24 hours (or less) of continuous therapy. Attempts to overcome tolerance by dose escalation, even to doses far in excess of those used acutely, have consistently failed. Only after nitrates have been absent from the body for several hours has their antianginal efficacy been restored.

The drug-free interval sufficient to avoid tolerance to isosorbide mononitrate has not been completely defined. In the only regimen of twice-daily isosorbide mononitrate that has been shown to avoid development of tolerance, the two doses of Isosorbide Mononitrate Tablets are given 7 hours apart, so there is a gap of 17 hours between the second dose of each day and the first dose of the next day. Taking account of the relatively long half-life of isosorbide mononitrate this result is consistent with those obtained for other organic nitrates.

The asymmetric twice-daily regimen of Isosorbide Mononitrate Tablets successfully avoided significant rebound/withdrawal effects. The incidence and magnitude of such phenomena have appeared, in studies of other nitrates, to be highly dependent upon the schedule of nitrate administration.

Pharmacokinetics:

Isosorbide mononitrate is rapidly and completely absorbed from the gastrointestinal tract. In humans, isosorbide mononitrate is not subject to first pass metabolism in the liver. The absolute bioavailability of isosorbide mononitrate from Isosorbide Mononitrate Tablets is nearly 100%. Peak plasma concentrations usually occur in about 30-60 minutes. Isosorbide mononitrate exhibits dose proportionality over the recommended dose range. Food does not significantly affect the absorption or bioavailability of Isosorbide Mononitrate Tablets. Metoprolol coadministration did not change the pharmacokinetics of isosorbide mononitrate. The volume of distribution is approximately 0.6 L/kg. Plasma protein binding of isosorbide mononitrate was found to be less than 5%.

When radiolabelled isosorbide mononitrate was administered to humans in order to elucidate the metabolic fate, about half of the dose was found denitrated and renally excreted as isosorbide and sorbitol. One quarter of the dose was accounted for as conjugates of the parent drug in the urine. None of these metabolites is vasoactive. Only 2% of the dose was excreted as unchanged drug.

The overall elimination half-life of isosorbide mononitrate is about 5 hours. The rate of clearance is the same in healthy young adults, in patients with various degrees of renal, hepatic or cardiac dysfunction and in the elderly. When radiolabelled isosorbide mononitrate was administered to humans, 93% of the dose was excreted within 48 hours into the urine. Renal excretion was virtually complete after 5 days; fecal excretion amounted to only 1% of the dose.

Isosorbide mononitrate has no known effect on renal and hepatic function. In patients with varying degrees of renal failure, dosage adjustment does not appear necessary. In patients with liver cirrhosis, the pharmacokinetic parameters after a single dose of isosorbide mononitrate were similar to the values found in healthy volunteers.

Isosorbide mononitrate is significantly removed from the blood during hemodialysis; however, an additional dose to compensate for drug lost is not necessary. In patients undergoing continuous ambulatory peritoneal dialysis, blood levels are similar to patients not on dialysis.

Clinical Trials:

The acute and chronic antianginal efficacy of isosorbide mononitrate has been confirmed in clinical trials. The clinical efficacy of isosorbide mononitrate was studied in 21 stable angina pectoris patients. After single dose administration of Isosorbide Mononitrate Tablets, 20 mg, the exercise capacity was increased by 42.7% after one hour, 29.6% after 6 hours, and by 25% after eight hours when compared to placebo. Controlled trials of single doses of Isosorbide Mononitrate Tablets have demonstrated that antianginal activity is present about 1 hour after dosing, with peak effect seen from 1-4 hours after dosing.

In one multicenter placebo-controlled trial, isosorbide mononitrate was found to be safe and effective during acute and chronic (3 weeks) treatment of angina pectoris. Two hundred fourteen (214) patients were enrolled in the trial; 54 patients were randomized to receive placebo and
106 patients were randomized to receive 10 or 20 mg of Isosorbide Mononitrate Tablets twice daily seven hours apart. The largest effect of isosorbide mononitrate, compared to placebo, was on day one - dose one. Although 14 hours after the first dose of day 14, the increase in exercise tolerance due to isosorbide mononitrate was statistically significant, the increase was about half of that seen 2 hours after the first dose of day one. On day 21, two hours after the first dose the effect of isosorbide mononitrate was 60 to 70% of that seen on day one.

INDICATIONS AND USAGE:

Isosorbide Mononitrate Tablets are indicated for the prevention and treatment of angina pectoris due to coronary artery disease. The onset of action of oral isosorbide mononitrate is not sufficiently rapid for this product to be useful in aborting an acute anginal episode.

CONTRAINDICATIONS:

Isosorbide mononitrate is contraindicated in patients who are allergic to it.

Do not use isosorbide mononitrate in patients who are taking certain drugs for erectile dysfunction (phosphodiesterase inhibitors), such as sildenafil, tadalafil, or vardenafil. Concomitant use can cause severe hypotension, syncope, or myocardial ischemia.

Do not use isosorbide mononitrate in patients who are taking the soluble guanylate cyclase stimulator riociguat. Concomitant use can cause hypotension.

WARNINGS:

Amplification of the vasodilatory effects of isosorbide mononitrate by sildenafil can result in severe hypotension. The time course and dose dependence of this interaction have not been studied. Appropriate supportive care has not been studied, but it seems reasonable to treat this as a nitrate overdose, with elevation of the extremities and with central volume expansion.

The benefits of isosorbide mononitrate in patients with acute myocardial infarction or congestive heart failure have not been established. Because the effects of isosorbide mononitrate are difficult to terminate rapidly, this drug is not recommended in these settings.

If isosorbide mononitrate is used in these conditions, careful clinical or hemodynamic monitoring must be used to avoid the hazards of hypotension and tachycardia.

PRECAUTIONS:

General:

Severe hypotension, particularly with upright posture, may occur with even small doses of isosorbide mononitrate. This drug should therefore be used with caution in patients who may be volume depleted or who, for whatever reason, are already hypotensive. Hypotension induced by isosorbide mononitrate may be accompanied by paradoxical bradycardia and increased angina pectoris.

Nitrate therapy may aggravate the angina caused by hypertrophic cardiomyopathy. In industrial workers who have had long-term exposure to unknown (presumably high) doses of organic nitrates, tolerance clearly occurs. Chest pain, acute myocardial infarction, and even sudden death have occurred during temporary withdrawal of nitrates from these workers, demonstrating the existence of true physical dependence. The importance of these observations to the routine, clinical use of oral isosorbide mononitrate is not known.

Information for Patients:

Patients should be told that the antianginal efficacy of Isosorbide Mononitrate Tablets can be maintained by carefully following the prescribed schedule of dosing (two doses taken seven hours apart). For most patients, this can be accomplished by taking the first dose on awakening and the second dose 7 hours later.

As with other nitrates, daily headaches sometimes accompany treatment with isosorbide mononitrate. In patients who get these headaches, the headaches are a marker of the activity of the drug. Patients should resist the temptation to avoid headaches by altering the schedule of their treatment with isosorbide mononitrate, since loss of headache may be associated with simultaneous loss of antianginal efficacy. Aspirin and/or acetaminophen, on the other hand, often successfully relieve isosorbide mononitrate-induced headaches with no deleterious effect on isosorbide mononitrate’s antianginal efficacy.

Treatment with isosorbide mononitrate may be associated with light-headedness on standing, especially just after rising from a recumbent or seated position. This effect may be more frequent in patients who have also consumed alcohol.

Drug Interactions:

Concomitant use of isosorbide mononitrate with phosphodiesterase inhibitors in any form is contraindicated (see CONTRAINDICATIONS).

Concomitant use of isosorbide mononitrate with riociguat, a soluble guanylate cyclase stimulator, is contraindicated (see CONTRAINDICATIONS).

The vasodilating effects of isosorbide mononitrate may be additive with those of other vasodilators. Alcohol, in particular, has been found to exhibit additive effects of this variety.

Marked symptomatic orthostatic hypotension has been reported when calcium channel blockers and organic nitrates were used in combination. Dose adjustments of either class of agents may be necessary.

Carcinogenesis, Mutagenesis, Impairment of Fertility:

No evidence of carcinogenicity was observed in rats exposed to isosorbide mononitrate in their diets at doses of up to 900 mg/kg/day for the first six months and 500 mg/kg/day for the remaining duration of a study in which males were dosed for up to 121 weeks and females were dosed for up to 137 weeks. No evidence of mutagenicity was seen in vitro in the Salmonella test (Ames test), in human peripheral lymphocytes, in Chinese hamster cells (V79) or, in vivo in the rat micronucleus test. In a study on the fertility and breeding capacity of two generations of rats, isosorbide mononitrate had no adverse effects on fertility or general reproductive performance with oral doses up to 120 mg/kg/day. A dose of 360 mg/kg/day was associated with increased mortality in treated males and females and a reduced fertility index. (See table at end of Pregnancysection for animal-to-human dosage comparisons.)

Pregnancy:

Teratogenic Effects:

Pregnancy Category B: Reproduction studies performed in rats and rabbits at doses of up to 540 and 810 mg/kg/day, respectively, have revealed no evidence of harm to the fetus due to isosorbide mononitrate. There are, however, no adequate and well-controlled studies in pregnant women. Because animal reproduction studies are not always predictive of human response, isosorbide mononitrate should be used during pregnancy only if clearly needed.

Nonteratogenic Effects:

Birth weights, neonatal survival and development, and incidence of stillbirths were adversely affected when pregnant rats were administered oral doses of 540 (but not 270) mg isosorbide mononitrate/kg/day during late gestation and lactation. This dose was associated with decreased maternal body weight gain and decreased maternal motor activity.

Species | Daily Dose; (mg/kg) | Multiple of MRHD* Based on:; Body Weight Body Surface
Rabbit | 810 | 1013 | 375
Rat | 900; 540; 500; 360; 270 | 1125; 675; 625; 450; 338 | 195; 117; 108; 78; 59

Calculations assume a human weight of 50 kg and human body surface area of 1.46 m^2, a rabbit weight of 2 kg and rabbit body surface area of 0.163 m^2, and a rat weight of 150 g and rat body surface area of 0.025 m^2. *Maximum recommended human dose (MRHD) is 20 mg bid.

Nursing Mothers:

It is not known whether isosorbide mononitrate is excreted in human milk. Because many drugs are excreted in human milk, caution should be exercised when isosorbide mononitrate is administered to a nursing woman.

Pediatric Use:

Safety and effectiveness of isosorbide mononitrate in pediatric patients have not been established.

Geriatric Use:

Clinical studies of isosorbide mononitrate did not include sufficient numbers of subjects aged 65 and over to determine whether they respond differently from younger subjects. Other reported clinical experience has not identified differences in responses between the elderly and younger patients. In general, dose selection for an elderly patient should be cautious, usually starting at the low end of the dosing range, reflecting the greater frequency of decreased hepatic, renal, or cardiac function, and of concomitant disease or other drug therapy.

ADVERSE REACTIONS:

To report SUSPECTED ADVERSE REACTIONS, contact Omnivium Pharmaceuticals LLC at 1-888-807-1048 or FDA at 1-800-FDA-1088 or www.fda.gov/medwatch.

Headache is the most frequent side effect and was the cause of 2% of all dropouts from controlled-clinical trials. Headache decreased in incidence after the first few days of therapy.

The following table shows the frequency of adverse reactions observed in 1% or more of subjects in 6 placebo-controlled trials, conducted in the United States and abroad. The same table shows the frequency of withdrawal for these adverse reactions. In many cases the adverse reactions were of uncertain relation to drug treatment.

Frequency of Adverse Reactions (Discontinuations)*
 | 6 Placebo-Controlled Studies
Dose | Placebo | 5 mg | 10 mg | 20 mg
Patients | 160 | 54 | 52 | 159
Headache | 6% (0%) | 17% (0%) | 13% (0%) | 35% (5%)
Fatigue | 2% (0%) | 0% (0%) | 4% (0%) | 1% (0%)
Upper Respiratory Infection | <1% (0%) | 0% (0%) | 4% (0%) | 1% (0%)
Pain | <1% (0%) | 4% (0%) | 0% (0%) | <1% (0%)
Dizziness | 1% (0%) | 0% (0%) | 0% (0%) | 4% (0%)
Nausea | <1% (0%) | 0% (0%) | 0% (0%) | 3% (2%)
Increased Cough | <1% (0%) | 0% (0%) | 2% (0%) | <1% (0%)
Rash | 0% (0%) | 2% (2%) | 0% (0%) | <1% (0%)
Abdominal Pain | <1% (0%) | 0% (0%) | 2% (0%) | 0% (0%)
Allergic Reaction | 0% (0%) | 0% (0%) | 2% (0%) | 0% (0%)
Cardiovascular Disorder | 0% (0%) | 2% (0%) | 0% (0%) | 0% (0%)
Chest Pain | <1% (0%) | 0% (0%) | 2% (0%) | <1% (0%)
Diarrhea | 0% (0%) | 0% (0%) | 2% (0%) | 0% (0%)
Flushing | 0% (0%) | 0% (0%) | 2% (0%) | 0% (0%)
Emotional Lability | 0% (0%) | 2% (0%) | 0% (0%) | 0% (0%)
Pruritus | 1% (0%) | 2% (2%) | 0% (0%) | 0% (0%)

*Some individuals discontinued for multiple reasons.

Other adverse reactions, each reported by fewer than 1% of exposed patients, and in many cases of uncertain relation to drug treatment, were:

Cardiovascular: acute myocardial infarction, apoplexy, arrhythmias, bradycardia, edema, hypertension, hypotension, pallor, palpitations, tachycardia.

Dermatologic: sweating.

Gastrointestinal: anorexia, dry mouth, dyspepsia, thirst, vomiting, decreased weight.

Genitourinary: prostatic disorder.

Miscellaneous: amblyopia, back pain, bitter taste, muscle cramps, neck pain, paresthesia, susurrus aurium.

Neurologic: anxiety, impaired concentration, depression, insomnia, nervousness, nightmares, restlessness, tremor, vertigo.

Respiratory: asthma, dyspnea, sinusitis.

Extremely rarely, ordinary doses of organic nitrates have caused methemoglobinemia in normal-seeming patients; for further discussion of its diagnosis and treatment see under Overdosage.

OVERDOSAGE:

Hemodynamic Effects:

The ill effects of isosorbide mononitrate overdose are generally the results of isosorbide mononitrate’s capacity to induce vasodilatation, venous pooling, reduced cardiac output, and hypotension. These hemodynamic changes may have protean manifestations, including increased intracranial pressure, with any or all of persistent throbbing headache, confusion, and moderate fever; vertigo; palpitations; visual disturbances; nausea and vomiting (possibly with colic and even bloody diarrhea); syncope (especially in the upright posture); air hunger and dyspnea, later followed by reduced ventilatory effort; diaphoresis, with the skin either flushed or cold and clammy; heart block and bradycardia; paralysis; coma; seizures and death.

Laboratory determinations of serum levels of isosorbide mononitrate and its metabolites are not widely available, and such determinations have, in any event, no established role in the management of isosorbide mononitrate overdose.

There are no data suggesting what dose of isosorbide mononitrate is likely to be life-threatening in humans. In rats and mice, there is significant lethality at oral doses of 1965 mg/kg and 2581 mg/kg, respectively.

No data are available to suggest physiological maneuvers (e.g., maneuvers to change the pH of the urine) that might accelerate elimination of isosorbide mononitrate. Isosorbide mononitrate is significantly removed from the blood during hemodialysis.

No specific antagonist to the vasodilator effects of isosorbide mononitrate is known, and no intervention has been subject to controlled study as a therapy of isosorbide mononitrate overdose. Because the hypotension associated with isosorbide mononitrate overdose is the result of venodilatation and arterial hypovolemia, prudent therapy in this situation should be directed toward an increase in central fluid volume. Passive elevation of the patient’s legs may be sufficient, but intravenous infusion of normal saline of similar fluid may also be necessary.

The use of epinephrine or other arterial vasoconstrictors in this setting is likely to do more harm than good.

In patients with renal disease or congestive heart failure, therapy resulting in central volume expansion is not without hazard. Treatment of isosorbide mononitrate overdose in these patients may be subtle and difficult, and invasive monitoring may be required.

Methemoglobinemia:

Methemoglobinemia has been reported in patients receiving other organic nitrates, and it probably could also occur as a side effect of isosorbide mononitrate. Certainly nitrate ions liberated during metabolism of isosorbide mononitrate can oxidize hemoglobin into methemoglobin. Even in patients totally without cytochrome b5 reductase activity, however, and even assuming that the nitrate moiety of isosorbide mononitrate is quantitatively applied to oxidation of hemoglobin, about 2 mg/kg of isosorbide mononitrate should be required before any of these patients manifests clinically significant (≥10%) methemoglobinemia. In patients with normal reductase function, significant production of methemoglobin should require even larger doses of isosorbide mononitrate. In one study in which 36 patients received 2-4 weeks of continuous nitroglycerin therapy at 3.1 to 4.4 mg/hr (equivalent, in total administered dose of nitrate ions, to 7.8 – 11.1 mg of isosorbide mononitrate per hour), the average methemoglobin level measured was 0.2%; this was comparable to that observed in parallel patients who received placebo.

Notwithstanding these observations, there are case reports of significant methemoglobinemia in association with moderate overdoses of organic nitrates. None of the affected patients had been thought to be unusually susceptible.

Methemoglobin levels are available from most clinical laboratories. The diagnosis should be suspected in patients who exhibit signs of impaired oxygen delivery despite adequate cardiac output and adequate arterial p02. Classically, methemoglobinemic blood is described as chocolate brown, without color change on exposure to air.

When methemoglobinemia is diagnosed, the treatment of choice is methylene blue, 1-2 mg/kg intravenously.

DOSAGE AND ADMINISTRATION:

The recommended regimen of Isosorbide Mononitrate Tablets is 20 mg twice daily, with the doses seven hours apart. A starting dose of 5 mg (½ tablet of the 10 mg dosing strength) might be appropriate for persons of particularly small stature but should be increased to at least 10 mg by the second or third day of therapy. Dosage adjustments are not necessary for elderly patients or patients with altered hepatic or renal function.

As noted above (Clinical Pharmacology), multiple studies of organic nitrates have shown that maintenance of continuous 24-hour plasma levels results in refractory tolerance. The asymmetric (2 doses, 7 hours apart) dosing regimen for Isosorbide Mononitrate Tablets provides a daily nitrate-free interval to minimize the development of tolerance.

As also noted under Clinical Pharmacology, well-controlled studies have shown that tolerance to Isosorbide Mononitrate Tablets occurs to some extent when using the twice-daily regimen in which the two doses are given seven hours apart. This regimen has been shown to have antianginal efficacy beginning one hour after the first dose and lasting at least seven hours after the second dose. The duration (if any) of antianginal activity beyond fourteen hours has not been studied.

In clinical trials, isosorbide mononitrate has been administered in a variety of regimens and doses. Doses above 20 mg twice a day (with the doses seven hours apart) have not been adequately studied. Doses of 5 mg twice a day are clearly effective (effectiveness based on exercise tolerance) for only the first day of a twice-a-day (with doses 7 hours apart) regimen.

HOW SUPPLIED:

Isosorbide Mononitrate 10 mg Tablets, USP are white, round, scored and engraved "10" on one side and engraved "KU 106" on the other. They are supplied as follows:

Bottles of 100 NDC 81665-102-10

Isosorbide Mononitrate 20 mg Tablets, USP are white, round, scored and engraved "20" on one side and engraved "KU 107" on the other. They are supplied as follows:

Bottles of 100 NDC 81665-103-10

Store at 20° - 30°C (68° - 86°F) [See USP]. Keep tightly closed.

Distributed by:
Omnivium Pharmaceuticals
Rahway, NJ 07065

CIB72212A

Rev. 06/2024